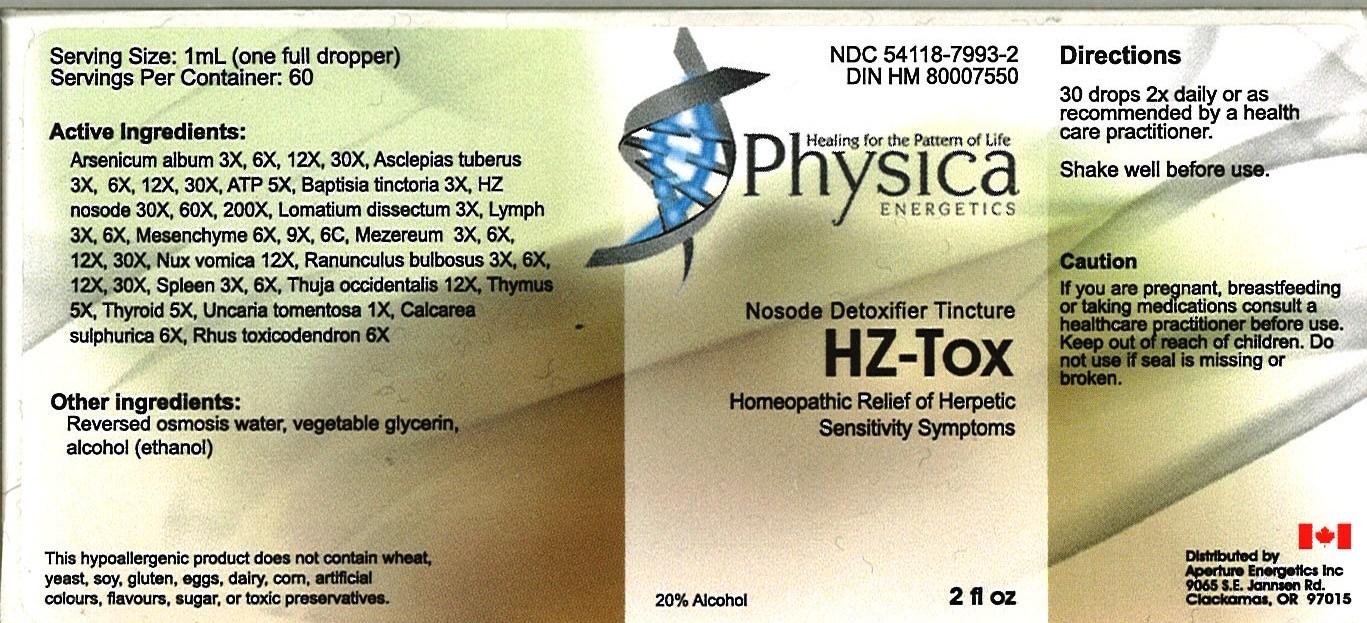 DRUG LABEL: HZ - Tox
NDC: 54118-7993 | Form: SOLUTION/ DROPS
Manufacturer: ABCO Laboratories, Inc
Category: homeopathic | Type: HUMAN OTC DRUG LABEL
Date: 20121221

ACTIVE INGREDIENTS: ARSENIC 3 [hp_X]/60 mL; ASCLEPIAS TUBEROSA FLOWERING TOP 3 [hp_X]/60 mL; ADENOSINE TRIPHOSPHATE 5 [hp_X]/60 mL; BAPTISIA TINCTORIA 3 [hp_X]/60 mL; HUMAN HERPESVIRUS 5 30 [hp_X]/60 mL; LOMATIUM DISSECTUM ROOT 3 [hp_X]/60 mL; BOS TAURUS LYMPH 3 [hp_X]/60 mL; BOS TAURUS MESENCHYME 6 [hp_X]/60 mL; DAPHNE MEZEREUM BARK 3 1/60 mL; STRYCHNOS NUX-VOMICA SEED 12 [hp_X]/60 mL; RANUNCULUS BULBOSUS 3 [hp_X]/60 mL; BOS TAURUS SPLEEN 3 [hp_X]/60 mL; THUJA OCCIDENTALIS LEAF 12 [hp_X]/60 mL; BOS TAURUS THYMUS 5 [hp_X]/60 mL; THYROID, BOVINE 5 [hp_X]/60 mL; CAT'S CLAW 1 [hp_X]/60 mL; CALCIUM SULFATE ANHYDROUS 6 [hp_X]/60 mL; TOXICODENDRON PUBESCENS LEAF 6 [hp_X]/60 mL
INACTIVE INGREDIENTS: WATER; GLYCERIN; ALCOHOL

HZ - Tox Homeopathic Liquid

Active Ingredients:

Arsenicum album 3x, 6x, 12x, 30x

Asclepias tuberus 3x, 6x, 12x, 30x

ATP 5x

Baptisia Tinctoria 3x

HZ nosode 30x, 60x, 200x

Lomatium Dissectum 3x

Lymph 3x, 6x

Mesenchyme 6x, 9x, 6c

Mezereum 3x, 6x, 12x, 30x

Nux Vomica 12x

Ranunculus bulbosus 3x, 6x, 12x, 30x

Spleen 3x, 6x

Thuja Occidentalis 12x

Thymus 5x

Thyroid 5x

Uncaria Tomentosa 1x

Calcarea Sulphurica 6x

Rhus Toxicodendron 6x

PURPOSE

- Homeopathic Relief of Herpetic Sensitivity Symptoms

- Keep out of reach of children

INDICATIONS AND USAGE

- 30 drops 2X daily in warm water or as recommended by a health care practitioner,
- Shake well before use.

WARNINGS

- If you are pregnant, breastfeeding or taking medications consult a healthcare practitioner before use,
- Keep out of reach of children,
- Do not use if seal is missing or broken.

DOSAGE AND ADMINISTRATION

- 30 drops 2X daily or as recommended by a health care practitioner,
- Shake well before use.

INACTIVE INGREDIENT

- Reverse osmosis water,
- vegetable glycerin,
- alcohol (ethanol).